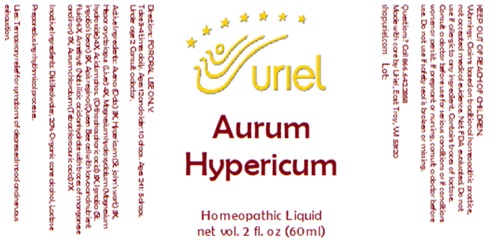 DRUG LABEL: Aurum Hypericum
NDC: 48951-1368 | Form: LIQUID
Manufacturer: Uriel Pharmacy Inc.
Category: homeopathic | Type: HUMAN OTC DRUG LABEL
Date: 20250819

ACTIVE INGREDIENTS: MAGNESIUM HYDROXIDE 4 [hp_X]/1 mL; STRYCHNOS IGNATII SEED 5 [hp_X]/1 mL; ROYAL JELLY 6 [hp_X]/1 mL; AVENA SATIVA FLOWERING TOP 3 [hp_X]/1 mL; PHOSPHORIC ACID 5 [hp_X]/1 mL; SILICON DIOXIDE 7 [hp_X]/1 mL; GOLD TRICHLORIDE 7 [hp_X]/1 mL; ST. JOHN'S WORT 3 [hp_X]/1 mL; MAMMAL LIVER 4 [hp_X]/1 mL
INACTIVE INGREDIENTS: WATER; ALCOHOL; LACTOSE, UNSPECIFIED FORM

Aurum Hypericum

INDICATIONS AND USAGE

Directions: FOR ORAL USE ONLY.

DOSAGE AND ADMINISTRATION

Take 3-4 times daily. Ages 12 and older: 10 drops.
Ages 2-11: 5 drops. Under age 2: Consult a doctor.

ACTIVE INGREDIENT

Active Ingredients: Avena (Oats) 3X, Hypericum (St. John’s Wort) 3X, Hepar oryctolagus (Liver) 4X, Magnesium hydroxydatum (Magnesium hydroxide) 4X, Acidum phos. (Orthosphoric acid) 5X, Ignatia (St. Ignatius’ bean) 5X, Apis regina (Queen Bee cell with larva and nutrient fluid) 6X, Amethyst (Nat. silicic acid anhydrate with traces of manganese and iron) 7X, Aurum chloratum (Tetrachloroauric acid) 7X

"prepared using rhythmical processes"

INACTIVE INGREDIENT

Inactive Ingredients: Distilled water, 20% Organic cane alcohol, Lactose

PURPOSE

Use: Temporary relief of headache.

KEEP OUT OF REACH OF CHILDREN.

WARNINGS

Warnings: Claims based on traditional homeopathic practice, not accepted medical evidence. Not FDA evaluated. Do not use if allergic to any ingredient. Consult a doctor before use for serious conditions or if conditions worsen or persist. Contains traces of lactose. If pregnant or nursing, consult a doctor before use. Do not use if safety seal is broken or missing.

Questions? Call 866.642.2858
Made with care by Uriel, East Troy, WI 53120
shopuriel.com